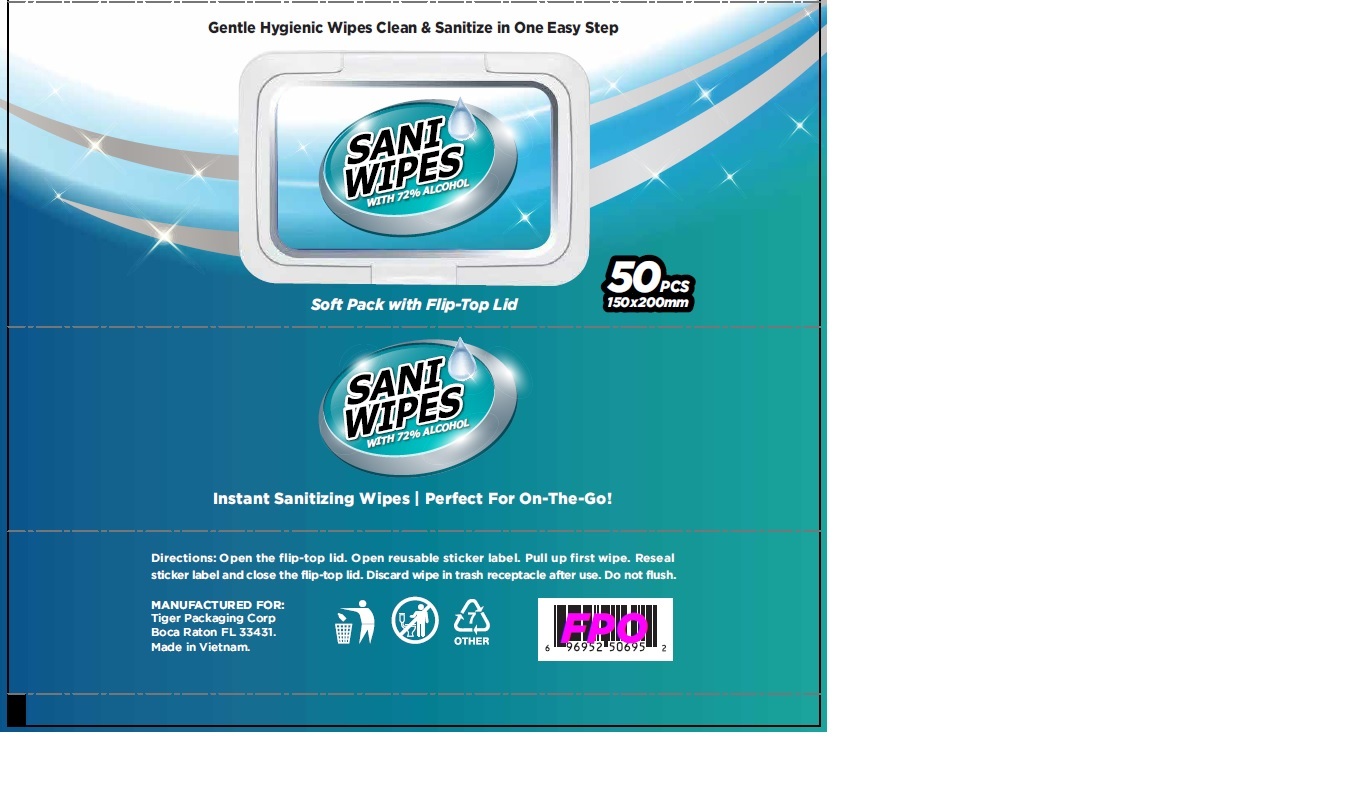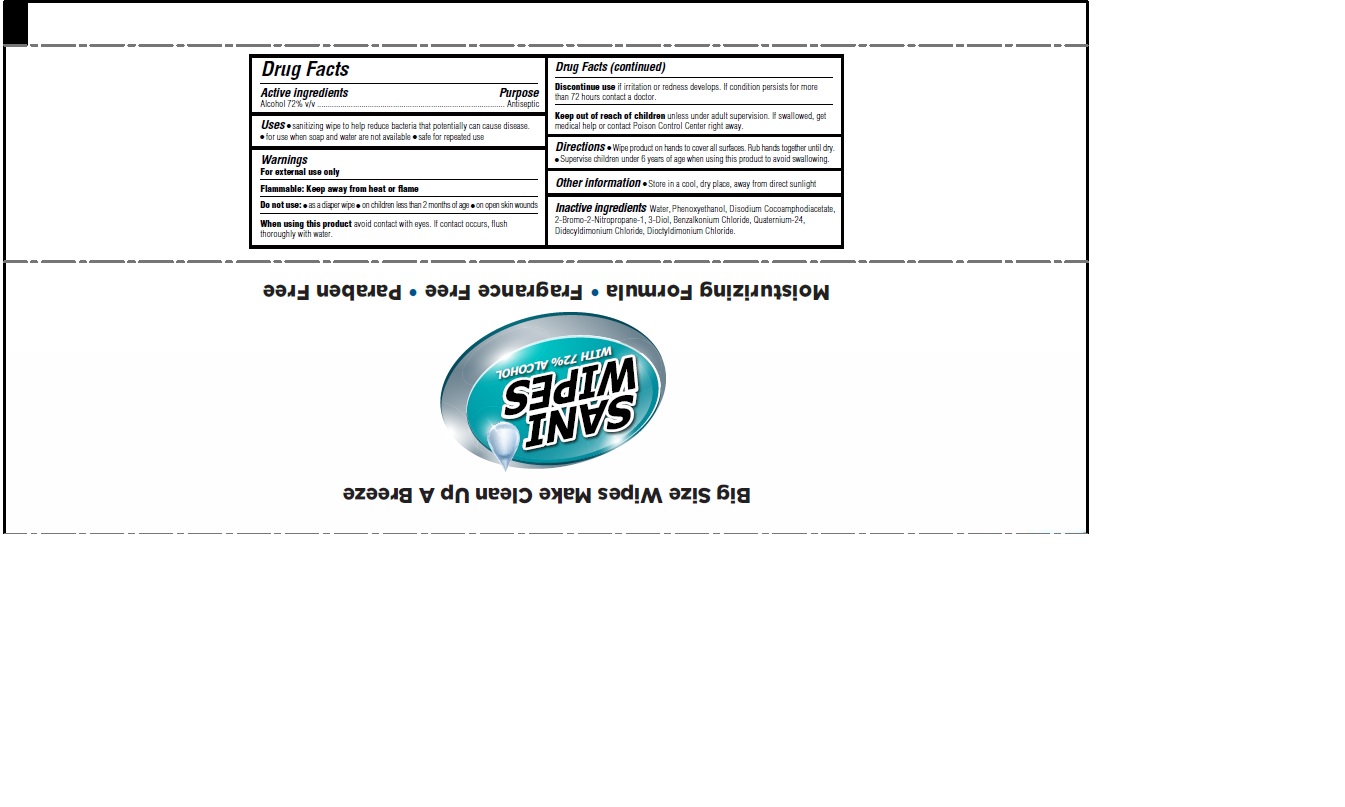 DRUG LABEL: SANI WIPES INSTANT SANITIZING WIPES
NDC: 77417-002 | Form: CLOTH
Manufacturer: Tiger Packaging Corp.
Category: otc | Type: HUMAN OTC DRUG LABEL
Date: 20220128

ACTIVE INGREDIENTS: ALCOHOL 72 mL/100 mL
INACTIVE INGREDIENTS: BRONOPOL; QUATERNIUM-24; DIDECYLDIMONIUM CHLORIDE; PHENOXYETHANOL; DISODIUM COCOAMPHODIACETATE; DIOCTYLDIMONIUM CHLORIDE; BENZALKONIUM CHLORIDE; WATER

Tiger Packaging Hand Sanitizer Wipes

Active ingredients

Alcohol 72% v/v

Purpose

Antiseptic

Uses

- sanitizing wipe to help reduce bacteria that potentially can cause disease.
- for use when soap and water are not available.
- safe for repeated use.

Warnings

For external use only.

Flammable. Keep away from heat or flame.

Do not use

- as a diaper wipe
- on children less than 2 months of age
- on open skin wounds

When using this product

avoid contact with eyes. If contact occurs, flush thoroughly with water.

Discontinue use

if irritation or redness develops. If condition persists for more than 72 hours contact a doctor.

Keep out of reach of children

unless under adult supervision. If swallowed, get medical help or contact a Poison Control Center right away.

Directions

- Wipe product on hands to cover all surfaces. Rub hands together until dry.
- Supervise children under 6 years of age when using this product to avoid swallowing.

Other information

- Store in a cool, dry place, away from direct sunlight

Inactive ingredients

Water, Phenoxyethanol, Disodium Cocoamphodiacetate, 2-Bromo-2-Nitropropane-1, 3-Diol, Benzalkonium Chloride, Quaternium-24, Didecyldimonium Chloride, Dioctyldimonium Chloride.

Company Information

MANUFACTURED FOR:

Tiger Packaging Corp

Boca Raton, FL 33431

Made in Vietnam

Product Packaging - 50 pcs

SANI WIPES

WITH 72% ALCOHOL

Instant Sanitizing Wipes

Perfect For On-The-Go!

50 PCS

150x200mm